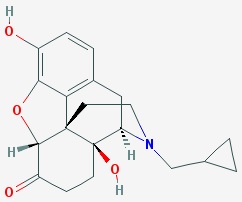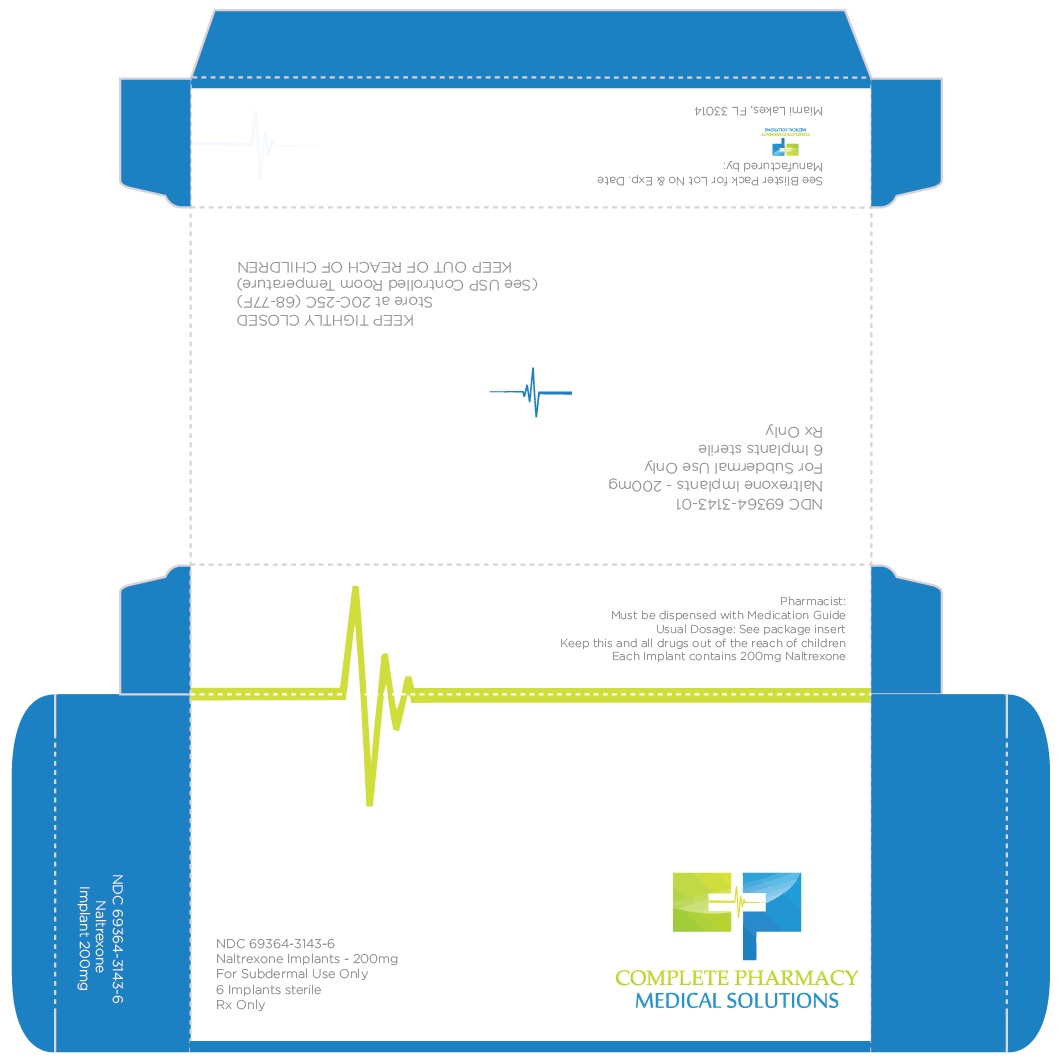 DRUG LABEL: Naltrexone
NDC: 69364-3143 | Form: IMPLANT
Manufacturer: Complete Pharmacy and Medical Solutions
Category: prescription | Type: HUMAN PRESCRIPTION DRUG LABEL
Date: 20180319

ACTIVE INGREDIENTS: NALTREXONE 200 mg/1 1; TRIAMCINOLONE 6.5 mg/1 1
INACTIVE INGREDIENTS: ASCORBIC ACID; STEARIC ACID; POVIDONE K30

Description

Naltrexone Implant
Formula:17-(Cyclopropilmethil)-4,5ª-Epoxy-3,14-dihidroximorfinan-6-ona

Formula molecular C20H23NO4C20H23NO4

Naltrexone Implants are supplied in a kit containing 6 X 200mg pellets, to be administered via a 4.5mm diameter trocar subcutaneously.

Additionally, each implant contains 3% triamcinolone as an active ingredient, as well as ascorbic acid, stearic acid, and polyvinylpyrrolidone as inactive ingredients.

Naltrexone implants are white, biconvex, with an elongated shape. Each Naltrexone 200mg implant is 0.215gm, with a diameter of 4.5mm and a length of 11mm.

Clinical Pharmacology

Mechanism of Action

Naltrexone is an opioid antagonist with highest affinity for the mµ opioid receptor. Naltrexone has few, if any, intrinsic actions besides its opioid blocking properties. However, it does produce some pupillary constriction, by an unknown mechanism.

The administration of naltrexone is not associated with the development of tolerance or dependence. In subjects physically dependent on opioids, naltrexone will precipitate withdrawal symptomatology.

Occupation of opioid receptors by naltrexone may block the effects of endogenous opioid peptides. The neurobiological mechanisms responsible for the reduction in alcohol consumption observed in alcohol-dependent patients treated with naltrexone are not entirely understood. However, involvement of the endogenous opioid system is suggested by preclinical data.

Naltrexone blocks the effects of opioids by competitive binding at opioid receptors. This makes the blockade produced potentially surmountable, but overcoming full naltrexone blockade by administration of opioids may result in non-opioid receptor mediated symptoms such as histamine release.

Naltrexone is not aversive therapy and does not cause a disulfiram-like reaction either as a result of opiate use or ethanol ingestion.

Pharmacokinetics

Absorption

Naltrexone Implants are intended to release over a 10-12 week period when administered subcutaneously. After implantation, the naltrexone plasma concentration time profile is characterized by an initial peak. Levels begin to decline slowly after dosing, with measurable levels for greater than 10-12weeks.

Distribution

In vitro data demonstrate that naltrexone plasma protein binding is low (21%).

Metabolism

Naltrexone is extensively metabolized in humans. Production of the primary metabolite, 6β-naltrexol, is mediated by dihydrodiol dehydrogenase, a cytosolic family of enzymes. The cytochrome P450 system is not involved in naltrexone metabolism. Two other minor metabolites are 2-hydroxy-3-methoxy-6β-naltrexol and 2-hydroxy-3-methoxy-naltrexone. Naltrexone and its metabolites are also conjugated to form glucuronide products.

Significantly less 6β-naltrexol is generated following subcutaneous administration of naltrexone compared to administration of oral naltrexone due to a reduction in first-pass hepatic metabolism.

Elimination

Elimination of naltrexone and its metabolites occurs primarily via urine, with minimal excretion of unchanged naltrexone.

Race: The effect of race on the pharmacokinetics of naltrexone implants has not been studied.

Pediatrics: The pharmacokinetics of naltrexone have not been evaluated in a pediatric population.

Drug-Drug Interactions

Clinical drug interaction studies with naltrexone implants have not been performed.
Naltrexone antagonizes the effects of opioid-containing medicines, such as cough and cold remedies, antidiarrheal preparations and opioid analgesics (see PRECAUTIONS).

Clinical Studies

Multiple studies have demonstrated an increase of adherence to drug and alcohol detox programs with extended release formulations.

The efficacy of naltrexone implants in the treatment of alcohol and various drug addiction was evaluated in a 12 week, placebo-controlled, multi-center, randomized trial in Mexico. Twenty-five subjects were treated with an implantation of 1200mg (6 X 200mg) Naltrexone. Oral naltrexone was not administered prior to the initial implantation. Psychological support was provided to all subjects on a weekly basis in addition to medication.

Subjects treated with naltrexone 1200mg implants demonstrated a greater reduction in days of heavy drinking and other substance abuse than those treated with placebo.

In another study published in the British Journal of Psychiatry, 56 patients at an addiction research center in Norway were given a naltrexone implant for treatment of heroin dependence. Researchers found that study participants who used the naltrexone implant for 180 days had an average of 45 fewer days of heroin use than members of the control group – and 60 fewer days of opioid use than members of the control group.

Similarly, a 2014 systematic review published in the Drug and Alcohol Review examined a variety of research results from 9 studies comparing naltrexone implant treatment to either oral naltrexone or to no treatment at all (a placebo).
Across the 9 studies, naltrexone implants were found to be:

- Significantly more effective than oral naltrexone.
- Significantly more effective than having no treatment at all.

Since the quality of these studies was evaluated as being “moderate to very low,” more research is still needed to better determine the effectiveness of naltrexone implants. However, the data so far suggests that naltrexone implants appear to improve addiction recovery success compared to taking naltrexone pills and compared to attempting to quit an addiction without any medication help.

Indications and Usage

Treatment with naltrexone implants should be part of a comprehensive management program that includes psychological and psychosocial support.

Naltrexone tablets were initially approved by the FDA in 1985 for the treatment of abuse and addiction of opioids.

Naltrexone in oral and extended release injection forms have been approved by the FDA for the treatment and abuse of alcohol.

Naltrexone implants may be useful for the treatment of alcohol or opioid dependence in patients who are able to abstain from opioid or alcohol in an outpatient setting prior to initiation of treatment.

Patients should not be actively drinking or be on any opioids at the time of initial naltrexone implant administration.

Dosage and Administration

Naltrexone implants must be administered by a physician.

To prevent occurrence of an acute abstinence syndrome (withdrawal) in patients dependent on opioids, or exacerbation of a pre-existing subclinical abstinence syndrome, opioid-dependent patients, including those being treated for alcohol dependence, must be opioid-free for a minimum of 7–10 days before starting Naltrexone Implant treatment. Since the absence of an opioid drug in the urine is often not sufficient proof that a patient is opioid-free, a naloxone challenge test should be employed if the prescribing physician feels there is a risk of precipitating a withdrawal reaction following administration of Naltrexone Implants. Patients treated for alcohol dependence with Naltrexone Implants should be assessed for underlying opioid dependence and for any recent use of opioids prior to initiation of treatment with Naltrexone Implants. Precipitated opioid withdrawal has been observed in alcohol-dependent patients in circumstances where the prescriber had been unaware of the additional use of opioids or dependence on opioids.

The aluminum (back) part of the blister packs should be wiped with sterile 70% isopropyl alcohol pads prior to opening. Implants should be handled via aseptic technique and should be used immediately.

The recommended dose of Naltrexone implants is 1200mg delivered subcutaneously every 10-12 weeks.

Reemergence of cravings should be screened and may be used as a gauge for the need for re-implantation schedule.

Healthcare providers should tailor the length of treatment to individual patients. Naltrexone has been administered to patients who are alcohol dependent for 6 months to 1 year with no additional safety concerns. Many scientists claim that treatment duration should last at least 1 year since this is the amount of time it can take to change the brain’s addiction pathways.

Treatment with Naltrexone should be part of a psychological and psychosocial program.

Laboratory Tests

Hepatic Enzymes

In short-term, controlled trials, in alcohol-dependent patients, the incidence of AST elevations associated with Naltrexone Injection treatment was similar to that observed with oral naltrexone treatment (1.5% each) and slightly higher than observed with placebo treatment (0.9%).

In the 6-month controlled trial conducted in opioid dependent subjects, 89% had a baseline diagnosis of hepatitis C infection, and 41% had a baseline diagnosis of HIV infection. There were frequently observed elevated liver enzyme levels (ALT, AST, and GGT); these were more commonly reported as adverse events in the naltrexone injection 380 mg group than in the placebo group. Patients could not enroll in this trial if they had a baseline ALT or AST value that was more than three times the upper limit of normal. More patients treated with naltrexone injection in this study experienced treatment-emergent elevations in transaminases to more than three times the upper limit of normal than patients treated with placebo. Shifts to more than three times the upper limit of normal occurred in 20% of patients treated with naltrexone injection as compared with 13% of placebo patients. Shifts in values of AST to more than three times the upper limit were also more common in the naltrexone injection (14%) arm compared with the placebo (11%) arm.

Opioid-dependent patients treated with naltrexone injection experienced a mean maximal increase from baseline ALT levels of 61 IU/L compared with 48 IU/L in placebo patients. Similarly for AST, opioid-dependent patients treated with naltrexone injection experienced a mean maximal increase from baseline AST levels of 40 IU/L compared with 31 IU/L in placebo patients.

Platelet Count.

Extended release Naltrexone formulations have reported a decrease in platelet count, although these reports were not associated with an increase in bleeding-related adverse events.

Creatinine Phosphokinase.

In short-term controlled trials in alcohol-dependent patients, more patients treated with Naltrexone Injection 380 mg (11%) and oral naltrexone (17%) shifted from normal creatinine phosphokinase (CPK) levels before treatment to abnormal CPK levels at the end of the trials, compared to placebo patients (8%). In open-label trials, 16% of patients dosed for more than 6 months had increases in CPK. For both the oral naltrexone and Naltrexone Injection 380 mg groups, CPK abnormalities were most frequently in the range of 1–2 x ULN. However, there were reports of CPK abnormalities as high as 4x ULN for the oral naltrexone group, and 35 x ULN for the Naltrexone Injection 380 mg group. Overall, there were no differences between the placebo and naltrexone (oral or injectable) groups with respect to the proportions of patients with a CPK value at least three times the upper limit of normal. No factors other than naltrexone exposure were associated with the CPK elevations.

More opioid-dependent patients treated with Naltrexone Injection 380 mg (39%) shifted from normal creatinine phosphokinase (CPK) levels before treatment to abnormal CPK levels during the study as compared to patients treated with placebo (32%). There were reports of CPK abnormalities as high as 41.8 x ULN for the placebo group, and 22.1 x ULN for the Naltrexone Injection 380 mg group.

Eosinophils.

Other extended release naltrexone formulations clinical trials have reported an increase in eosinophil counts, although continued use of these formulations reverted to normal over a period of several months.

Pharmacogenetics

A naltrexone treatment study by Anton et al., released by the National Institutes of Health in February 2008 and published in the Archives of General Psychiatry, has shown that alcoholics having a certain variant of the opioid receptor gene (G polymorphism of SNP Rs1799971 in the gene OPRM1), known as Asp40, demonstrated strong response to naltrexone and were far more likely to experience success at cutting back or discontinuing their alcohol intake altogether, while for those lacking the gene variant, naltrexone appeared to be no different from placebo. The G allele of OPRM1 is most common in individuals of Asian descent, with 60% to 70% of people of Chinese, Japanese, and Indian ancestry having at least one copy, as opposed to 30% of Europeans and few Africans.

Because of the characteristics of the patient group in the US, the first study was done on white patients and the next without regard for ethnicity. Anton et al. found that patients of African descent did not have much success with naltrexone in treatment for alcohol dependence because of lacking the relevant gene.

As white patients with the gene had a five times greater rate of success in reducing drinking when given naltrexone than did patients without the gene, when used in a protocol of Medical Management (MM), Anton et al. concluded,

"Because almost 25% of the treatment-seeking population carries the Asp40 allele, genetic testing of individuals before naltrexone treatment might be worth the cost and effort, especially if structured behavioral treatment were not being considered."[30] This would enable treatment to be targeted by genetics to patients for whom it would be most effective. They noted, "Naltrexone is relatively easy to administer and free of serious adverse effects and, as we observed in the Asp40 carriers we studied, it appears to be highly effective."

Studies have found naltrexone to be more efficacious among certain white subjects, because of the genetic basis, than among black subjects, who generally do not carry the relevant gene variant. A 2009 study of naltrexone as an alcohol dependence treatment among African Americans failed to find any statistically significant differences between naltrexone and a placebo. Studies have suggested that carriers of the G allele may experience higher levels of craving and stronger "high" upon alcohol consumption, compared to carriers of the dominant allele, and naltrexone somewhat blunts these responses, leading to a reduction in alcohol use in some studies.

Warnings and Precautions

Hepatoxicity

Naltrexone has the capacity to cause hepatocellular injury when given in excessive doses.
Naltrexone is contraindicated in acute hepatitis or liver failure, and its use in patients with active liver disease must be carefully considered in light of its hepatotoxic effects.

The margin of separation between the apparently safe dose of naltrexone and the dose causing hepatic injury appears to be only five-fold or less. Naltrexone implants do not appear to be a hepatotoxin at the recommended doses.

Patients should be warned of the risk of hepatic injury and advised to seek medical attention if they experience symptoms of acute hepatitis. Use of Naltrexone implants should be discontinued in the event of symptoms and/or signs of acute hepatitis.

Implant Site Reactions

Infection and pellet extrusion are possible. Patients should be advised to avoid bath tubs and hot tubs, swimming, or exercise for 7 days after implantation to minimize extrusion risks. Infections must be reported to physicians and be treated with antibiotics.

Unintended Opiate Withdrawal

To prevent occurrence of an acute abstinence syndrome (withdrawal) in patients dependent on opioids, or exacerbation of a pre-existing subclinical abstinence syndrome, opioid-dependent patients, including those being treated for alcohol dependence, must be opioid-free for a minimum of 7–10 days before starting Naltrexone Implant treatment. Since the absence of an opioid drug in the urine is often not sufficient proof that a patient is opioid-free, a naloxone challenge test should be employed if the prescribing physician feels there is a risk of precipitating a withdrawal reaction following administration of Naltrexone Implants. Patients treated for alcohol dependence with Naltrexone Implants should be assessed for underlying opioid dependence and for any recent use of opioids prior to initiation of treatment with Naltrexone Implants. Precipitated opioid withdrawal has been observed in alcohol-dependent patients in circumstances where the prescriber had been unaware of the additional use of opioids or dependence on opioids.

Opioid Withdrawal at End of a Dosing Interval, After Missing a dose and Following an Attempt to Overcome Opioid Blockade

After opioid detoxification, patients are likely to have reduced tolerance to opioids. Although Naltrexone Implants blocks the effects of exogenous opioids for 10-12 weeks after administration, cases of opioid overdose with fatal outcomes have been reported in patients who used opioids at the end of a dosing interval with longer acting Naltrexone dosage forms or when missing a dose. Patients who have been treated with Naltrexone Implants may respond to lower doses of opioids than previously used. This could result in potentially life-threatening opioid intoxication (respiratory compromise or arrest, circulatory collapse, etc.).

Patients should be aware that they may be more sensitive to lower doses of opioids after Naltrexone Implant treatment is discontinued. Reduced tolerance is especially of concern at the end of a dosing interval, that is, near the end of the dosing cycle after the Naltrexone Implant was administered, or after a dose of Naltrexone Implant is missed. It is important that patients inform family members and the people closest to the patient of this increased sensitivity to opioids and the risk of overdose.

There is also the possibility that a patient who is treated with Naltrexone Implants could overcome the opioid blockade effect of Naltrexone. Although Naltrexone is a potent antagonist with a prolonged pharmacological effect, the blockade produced by Naltrexone is surmountable. This poses a potential risk to individuals who attempt, on their own, to overcome the blockade by administering large amounts of exogenous opioids. Any attempt by a patient to overcome the antagonism by taking opioids is very dangerous and may lead to fatal overdose. Injury may arise because the plasma concentration of exogenous opioids attained immediately following their acute administration may be sufficient to overcome the competitive receptor blockade. As a consequence, the patient may be in immediate danger of suffering life-endangering opioid intoxication (e.g., respiratory arrest, circulatory collapse). Patients should be told of the serious consequences of trying to overcome the opioid blockade.

Depression and Suicidality

Alcohol and opioid-dependent patients, including those taking Naltrexone Implants, should be monitored for the development of depression or suicidal thinking. Families and caregivers of patients being treated with Naltrexone Implants should be alerted to the need to monitor patients for the emergence of symptoms of depression or suicidality, and to report such symptoms to the patient’s healthcare professional.

Subdermal Implants

As with any procedure, Naltrexone Implants should be administered with caution to patients with thrombocytopenia or any coagulation disorder (e.g., hemophilia and severe hepatic failure).

When Reversal of Naltrexone Implants is Required for Pain Management

In an emergency situation in patients receiving Naltrexone Implants, suggestions for pain management include regional analgesia or use of non-opioid analgesics. If opioid therapy is required as part of anesthesia or analgesia, patients should be continuously monitored in an anesthesia care setting by persons not involved in the conduct of the surgical or diagnostic procedure. The opioid therapy must be provided by individuals specifically trained in the use of anesthetic drugs and the management of the respiratory effects of potent opioids, specifically the establishment and maintenance of a patent airway and assisted ventilation.

Irrespective of the drug chosen to reverse the Naltrexone blockade, the patient should be monitored closely by appropriately trained personnel in a setting equipped and staffed for cardiopulmonary resuscitation.

Substance Use Withdrawal

Use of Naltrexone Implants does not eliminate or diminish substance abuse withdrawal symptoms.

Interference with Laboratory Tests

Naltrexone may be cross-reactive with certain immunoassay methods for the detection of drugs of abuse (specifically opioids) in urine.

Contraindications

Naltrexone is contraindicated in:

- Patients receiving opioid analgesics (see PRECAUTIONS).
- Patients with current physiologic opioid dependence (see WARNINGS).
- Patients in acute opiate withdrawal (see WARNINGS).
- Any individual who has failed the naloxone challenge test or has a positive urine screen for opioids.
- Patients who have previously exhibited hypersensitivity to naltrexone, PVP, triamcinolone, or any other components of the diluent.

Adverse Effects

Naltrexone may cause side effects including:

- A reaction at the implant site. The reaction could be pain, tenderness, swelling, redness, and/or itching.
- Nausea

The other common side effects of Naltrexone are:

- Headache
- Fatigue
- Dizziness
- Vomiting
- Decreased appetite
- Painful joints
- Muscle cramps

These are not all of the side effects of naltrexone.

Drug Interactions

Patients taking naltrexone may not benefit from opioid-containing medicines (see PRECAUTIONS, Pain Management).

Because naltrexone is not a substrate for CYP drug metabolizing enzymes, inducers or inhibitors of these enzymes are unlikely to change the clearance of naltrexone. No clinical drug interaction studies have been performed with naltrexone to evaluate drug interactions, therefore prescribers should weigh the risks and benefits of concomitant drug use.

Carcinogenesis, Mutagenesis, Impairment of Fertility

Carcinogenicity studies have not been conducted with naltrexone implants.

Carcinogenicity studies of oral naltrexone hydrochloride (administered via the diet) have been conducted in rats and mice. In rats, there were small increases in the numbers of testicular mesotheliomas in males and tumors of vascular origin in males and females. The clinical significance of these findings is not known.

Naltrexone was negative in the following in vitro genotoxicity studies: bacterial reverse mutation assay (Ames test), the heritable translocation assay, CHO cell sister chromatid exchange assay, and the mouse lymphoma gene mutation assay. Naltrexone was also negative in an in vivo mouse micronucleus assay. In contrast, naltrexone tested positive in the following assays: Drosophila recessive lethal frequency assay, non-specific DNA damage in repair tests with E. coli and WI-38 cells, and urinalysis for methylated histidine residues.

Naltrexone given orally caused a significant increase in pseudopregnancy and a decrease in pregnancy rates in rats at 100 mg/kg/day (600 mg/m2/day). There was no effect on male fertility at this dose level. The relevance of these observations to human fertility is not known.

Pregnancy Category C

Reproduction and developmental studies have not been conducted for naltrexone implants.
Studies with naltrexone administered via the oral route have been conducted in pregnant rats and rabbits.

PREGNANCY

Teratogenic Effects: Oral naltrexone has been shown to increase the incidence of early fetal loss in rats administered ≥ 30 mg/kg/day (180 mg/m2/day) and rabbits administered ≥ 60 mg/kg/day (720 mg/m2/day).

There are no adequate and well-controlled studies of either naltrexone or naltrexone implants in pregnant women.

Labor and Delivery

The potential effect of naltrexone implants on duration of labor and delivery in humans is unknown.

Nursing Mothers

Transfer of naltrexone and 6β-naltrexol into human milk has been reported with oral naltrexone. Because of the potential for tumorigenicity shown for naltrexone in animal studies, and because of the potential for serious adverse reactions in nursing infants from naltrexone, a decision should be made whether to discontinue nursing or to discontinue the drug, taking into account the importance of the drug to the mother.

Pediatric Use

The safety and efficacy of naltrexone implants have not been established in the pediatric population.

Geriatric use

Clinical studies of naltrexone implants did not include sufficient numbers of subjects age 65 and over to determine whether they respond differently from younger subjects.

How Supplied

Naltrexone implants are available in a box of 6 X 200mg Naltrexone implants. Each implant is individually blister packed.

Storage

Store at 20° to 25°C (68° to 77°F); excursions permitted to 15° to 30°C (59° to 86°F). Naltrexone implants should be implanted before their date of expiration to assure sterility requirements.

Naltrexone Implant Patient Information

What is Naltrexone Implant?

- Naltrexone blocks the effects of narcotic medicines and alcohol.
- Naltrexone implants are used to treat addiction to alcohol or narcotic drugs. It is also used to prevent narcotic addiction relapse.
- Naltrexone Implants prevents the reward effects of opioids and alcohol with subsequent use.
- Craving decrease substantially in those people on naltrexone, and that this craving reduction occurs very quickly, from the beginning of treatment (first 2-3 weeks) and doesn’t seem to return after that. There are certainly people who continue to have cravings, but this is a rather small proportion and usually occurs only after coming off medication. Those who maintain treatment with naltrexone have no cravings, and some believe that combining naltrexone with personal recovery work in a 12-step based program is especially effective.
- Naltrexone implants may also be used for purposes not listed in this medication guide.

What are the possible side effects of naltrexone implant?

Get emergency medical help if you have any of these signs of an allergic reaction: hives; difficulty breathing; swelling of your face, lips, tongue, or throat.

Call your doctor at once if you have any of these serious side effects:

- Blurred vision or eye problems
- Fast heartbeat
- Wheezing, difficulty breathing
- Mood changes, hallucinations (seeing or hearing things), confusion, thoughts of hurting yourself
- Nausea, stomach pain, low fever, loss of appetite, dark urine, clay-colored stools, jaundice (yellowing of the skin or eyes)
- Ear pain, ringing in your ears
- Feeling light-headed, fainting
- Skin rash or itching
- Pain, redness, bruising, itching, swelling, oozing, skin changes, or a hard lump where the medication was implanted

Less serious side effects may include:

- Feeling anxious, nervous, restless, or irritable
- Increased thirst
- Muscle or joint aches
- Weakness or tiredness
- Sleep problems (insomnia)
- Decreased sex drive, impotence, or difficulty having an orgasm.

This is not a complete list of side effects and others may occur. Call your doctor for medical advice about side effects. You may report side effects to FDA at 1-800-FDA-1088.

What is the most important information I should know about naltrexone implants?

- Do not use narcotic drugs or alcohol while you are being treated with naltrexone implants. Never try to overcome the effects of the medication by using large doses of narcotic drugs or alcohol. Doing so could result in dangerous effects, including coma and death. Ask your doctor before using any prescription or over-the-counter medicine to treat a cold, cough, diarrhea, or pain during your treatment with naltrexone injection. These medicines may contain narcotics or alcohol.
- Use of Naltrexone Implants does not eliminate or diminish substance abuse withdrawal symptoms.
- Naltrexone implants may impair your thinking or reactions. Be careful if you drive or do anything that requires you to be alert.
- You may notice pain, redness, bruising, swelling, or a hard lump where the medication was implanted. Call your doctor if you have this type of reaction to the implant, especially if it does not clear up or gets worse within 2 weeks.
- Wear a medical alert tag or carry an ID card stating that you use naltrexone implants. Any medical care provider who treats you should know that you are receiving this medication.
- Alert your healthcare professional right away if you develop serious bouts of depression or suicidal thinking.
- Families and caregivers of patients being treated with Naltrexone Implants should be alerted to the need to monitor patients for the emergence of symptoms of depression or suicidality, and to report such symptoms to the patient’s healthcare professional.
- Additional forms of counseling and/or monitoring may be recommended during treatment with naltrexone implants.
- You may be more sensitive to lower doses of opioids after Naltrexone Implant treatment is discontinued. Reduced tolerance is especially of concern at the end of a dosing interval, that is, near the end of the dosing cycle after the Naltrexone Implant was administered, or after a dose of Naltrexone Implant is missed. It is also important that you inform family members and the people closest to you of this increased sensitivity to opioids and the risk of overdose.

What should I discuss with my healthcare provider before receiving naltrexone implants?

Do not receive this implant if you are allergic to naltrexone, polyvinylpyrrolidone, stearic acid, ascorbic acid, triamcinolone or if you have:

- A history of alcohol or narcotic drug use within the past 7-10 days; or
- Drug or alcohol withdrawal symptoms.

To make sure you can safely use naltrexone implant, tell your doctor if you have any of these other conditions:

- Kidney disease
- Liver disease
- A bleeding disorder such as hemophilia
- FDA pregnancy category C. It is not known whether naltrexone implant will harm an unborn baby. Tell your doctor if you are pregnant or plan to become pregnant while using this medication.
- It is not known whether naltrexone implant passes into breast milk or if it could harm a nursing baby. Do not use this medication without telling your doctor if you are breast-feeding a baby.

How is the Naltrexone Implant Used?

- Naltrexone implants are placed under the skin. The implants are usually given once every 3 months (every 10-12 weeks) and can be given only by a doctor in a clinic.
- It is important to receive your naltrexone implants regularly to get the most benefit.
- Avoid bath tubs and hot tubs, swimming or exercise for 7 days after implantation to minimize risk of the implant coming out.
- You may notice pain, redness, bruising, swelling, or a hard lump where the medication was implanted. Call your doctor if you have this type of reaction to the implant, especially if it does not clear up or gets worse within 2 weeks.
- Wear a medical alert tag or carry an ID card stating that you use naltrexone implants. Any medical care provider who treats you should know that you are receiving this medication.
- Additional forms of counseling and/or monitoring may be recommended during treatment with naltrexone injection.

What happens if I miss a dose?

- Call your doctor for instructions if you miss an appointment to receive your naltrexone implant.

What happens if I overdose?

- Seek emergency medical attention or call the Poison Help line at 1-800-222-1222.
- Overdose symptoms may include nausea, stomach pain, dizziness, or seizure (convulsions).

What should I avoid while using Naltrexone Implants?

- Naltrexone may impair your thinking or reactions. Be careful if you drive or do anything that requires you to be alert.
- Do not use narcotic drugs or alcohol while receiving naltrexone implants. Never try to overcome the effects of the medication by using large doses of narcotic drugs or alcohol. Doing so could result in dangerous effects, including coma and death. Ask your doctor before using any prescription or over-the-counter medicine to treat a cold, cough, diarrhea, or pain while you are being treated with naltrexone implants. These medicines may contain narcotics or alcohol.

What other drugs will affect naltrexone implants?

The pain-relieving effects of any narcotic pain medications you use will be blocked if you use them during your treatment with naltrexone implants. Harmful side effects could also occur.

Tell your doctor about all other medicines you use, especially:

- Buprenorphine (Buprenex, Subutex)
- Butorphanol (Stadol)
- Codeine (Tylenol with Codeine)
- Hydrocodone (Lortab, Vicodin)
- Hydromorphone (Dilaudid)
- Levorphanol (Levo-Dromoran)
- Meperidine (Demerol)
- Methadone (Dolophine, Methadose)
- Morphine (Kadian, MS Contin, Roxanol)
- Nalbuphine (Nubain)
- Naloxone (Narcan)
- Oxycodone (Oxycontin, Roxicodone, Percocet)
- Oxymorphone (Numorphan)
- Propoxyphene (Darvon, Darvocet)

This list is not complete and other drugs may interact with naltrexone implants. Tell your doctor about all medications you use. This includes prescription, over-the-counter, vitamin, and herbal products. Do not start a new medication without telling your doctor.

Where can I get more information?

- Your doctor can provide more information about naltrexone implants.